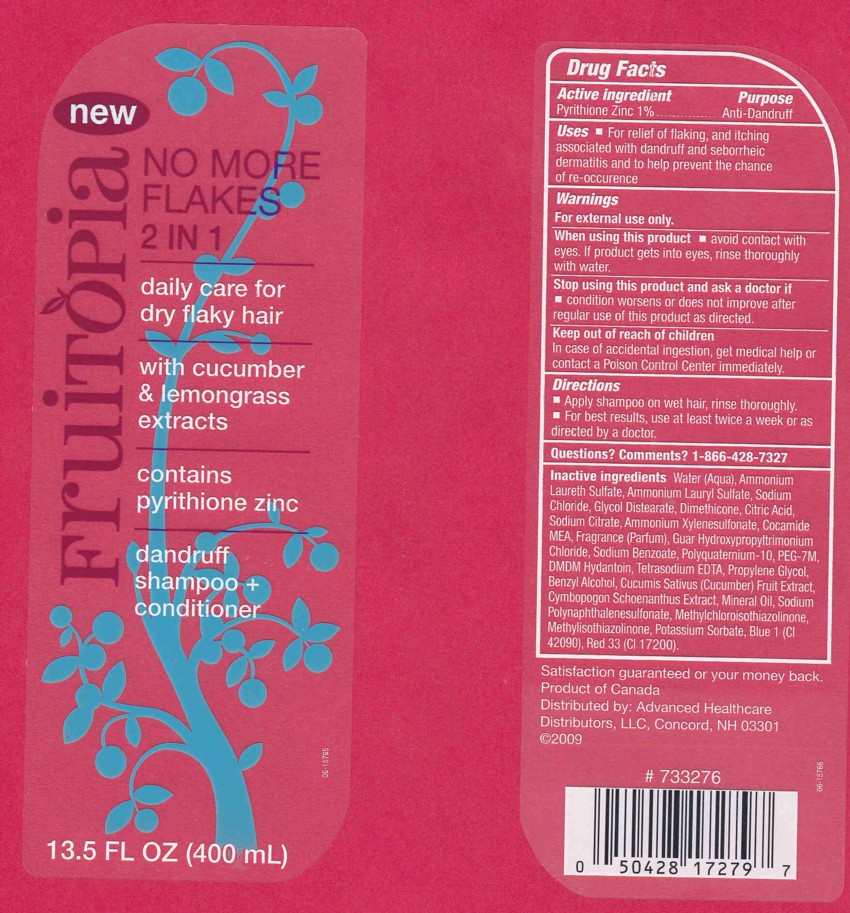 DRUG LABEL: DANDRUFF SHAMPOO AND CONDITIONER 
NDC: 63148-418 | Form: LOTION/SHAMPOO
Manufacturer: APOLLO HEALTH AND BEAUTY CARE
Category: otc | Type: HUMAN OTC DRUG LABEL
Date: 20100308

ACTIVE INGREDIENTS: PYRITHIONE ZINC 1.0000 mL/100 mL
INACTIVE INGREDIENTS: SODIUM CITRATE 0.5000 mL/100 mL

Dandruff Shampoo and Conditioner

ACTIVE INGREDIENT

PYRITHIONE ZINC 1% (ANTI - DANDRUFF)

USES

For relief of flaking, and itching associated with dandruff and seborrheic dermatitis and to help prevent the chance of re - occurence

WARNINGS

FOR EXTERNAL USE ONLY

WHEN USING THIS PRODUCT

AVOID CONTACT WITH EYES. IF CONTACT OCCURS, RINSE EYES THROUGHLY WITH WATER.

STOP USE AND ASK A DOCTOR IF

CONDITION WORSENS OR DOES NOT IMPROVE AFTER REGULAR USE OF THIS PRODUCT AS DIRECTED

KEEP OUT OF REACH OF CHILDREN

IF SWALLOWED, GET MEDICAL HELP OR CONTACT POISON CONTROL CENTER IMMEDIATELY.

QUESTIONS?

CALL 1-866-428-7327

PACKAGE FRONT AND BACK LABELS

- FRONT AND BACK LABELS: fruitopia14.jpg